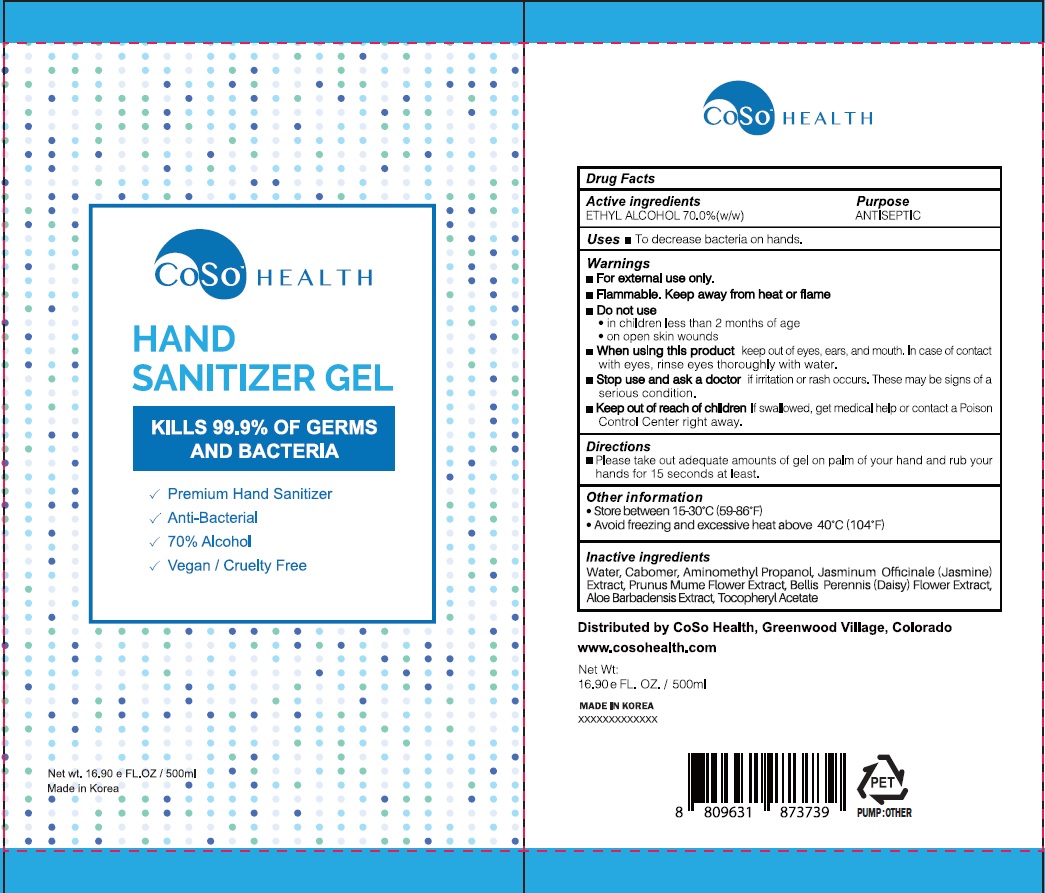 DRUG LABEL: CoSo HEALTH HAND SANITIZER
NDC: 75010-100 | Form: GEL
Manufacturer: Mirfeel Korea Co., Ltd
Category: otc | Type: HUMAN OTC DRUG LABEL
Date: 20200804

ACTIVE INGREDIENTS: Alcohol 350 g/500 mL
INACTIVE INGREDIENTS: Water; CARBOMER HOMOPOLYMER, UNSPECIFIED TYPE; AminomethylPropanol; JASMINUM OFFICINALE FLOWER; PRUNUS MUME FLOWER; BELLIS PERENNIS FLOWER; ALOE VERA LEAF; .ALPHA.-TOCOPHEROL ACETATE

ACTIVE INGREDIENT

Ethyl alcohol 70%(w/w)

INACTIVE INGREDIENT

Water, Carbomer, Aminomethyl Propanol, Jasminum Officinale (Jasmine) Extract, Prunus Mume Flower Extract, Bellis Perennis (Daisy) Flower Extract, Aloe Barbadensis Extract, Tocopheryl Acetate

PURPOSE

ANTISEPTIC

WARNINGS

ㆍFor external use only.
ㆍFlammable. Keep away from fire or flame

ㆍDo not use
-in children less than 2 months of age
-on open skin wounds

ㆍWhen using this product keep out of eyes, ears, and mouth. In case of contact with eyes, rins eyes thoroughly with water.

ㆍStop use and ask a doctor if irritation or rash occurs. These may be signs of a serious condition.

ㆍKeep out of reach of children if swallowed, get medical help or contact a Poison Control Center right away.

KEEP OUT OF REACH OF CHILDREN

If swallowed, get medical help or contact a Poison Control Center right away.

Uses

ㆍTo decrease bacteria on hands.

Directions

ㆍPlease take out adequate amounts of gel on palm of your hand and rub your hands for 15 seconds at least.

Other Information

ㆍStore between 15-30℃ (59-86℉)
ㆍAvoid freezing and excessive heat above 40℃ (104℉)